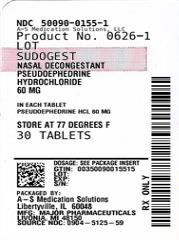 DRUG LABEL: SudoGest
NDC: 50090-0155 | Form: TABLET, FILM COATED
Manufacturer: A-S Medication Solutions
Category: otc | Type: HUMAN OTC DRUG LABEL
Date: 20210414

ACTIVE INGREDIENTS: PSEUDOEPHEDRINE HYDROCHLORIDE 60 mg/1 1
INACTIVE INGREDIENTS: HYPROMELLOSE, UNSPECIFIED; MAGNESIUM STEARATE; POLYETHYLENE GLYCOL, UNSPECIFIED; SILICON DIOXIDE; STEARIC ACID; MICROCRYSTALLINE CELLULOSE; STARCH, CORN; LACTOSE, UNSPECIFIED FORM

SudoGest
Nasal Decongestant

Active ingredient (in each tablet)

Pseudoephedrine HCl 60 mg

Purpose

Nasal decongestant

Uses

- temporarily relieves nasal congestion due to the common cold, hay fever or other upper respiratory allergies
- temporarily relieves sinus congestion and pressure

Warnings

Do not use

if you are now taking a prescription monoamine oxidase inhibitor (MAOI) (certain drugs for depression, psychiatric or emotional conditions, or Parkinson's disease), or for 2 weeks after stopping the MAOI drug. If you do not know if your prescription drug contains an MAOI, ask a doctor or pharmacist before taking this product.

Ask a doctor before use if you have

- diabetes
- heart disease
- high blood pressure
- thyroid disease
- trouble urinating due to an enlarged prostate gland

When using this product

do not exceed recommended dose.

Stop use and ask a doctor if

- nervousness, dizziness, or sleeplessness occur
- symptoms do not improve within 7 days or occur with fever

If pregrant or breast-feeding,

ask a health professional before use.

Keep out of reach of children.

In case of overdose, get medical help or contact a Poison Control Center right away.

Directions

- adults and children 12 years and older: take 1 tablet every 4 to 6 hours. Do not take more than 4 tablets in 24 hours.
- children under 12 years of age: do not use

Other information

- store at 25ºC (77ºF); excursions permitted between 15˚-30˚C (59˚-86˚F)
- use by expiration date on package

Inactive ingredients

corn starch, hypromellose, lactose, magnesium stearate, microcrystalline cellulose, polyethylene glycol, silicon dioxide, stearic acid

Questions or comments?

(800) 616-2471

HOW SUPPLIED

Product: 50090-0155

NDC: 50090-0155-1 30 TABLET, FILM COATED in a BOTTLE

NDC: 50090-0155-3 12 TABLET, FILM COATED in a BOTTLE

NDC: 50090-0155-4 20 TABLET, FILM COATED in a BOTTLE

NDC: 50090-0155-5 15 TABLET, FILM COATED in a BOTTLE